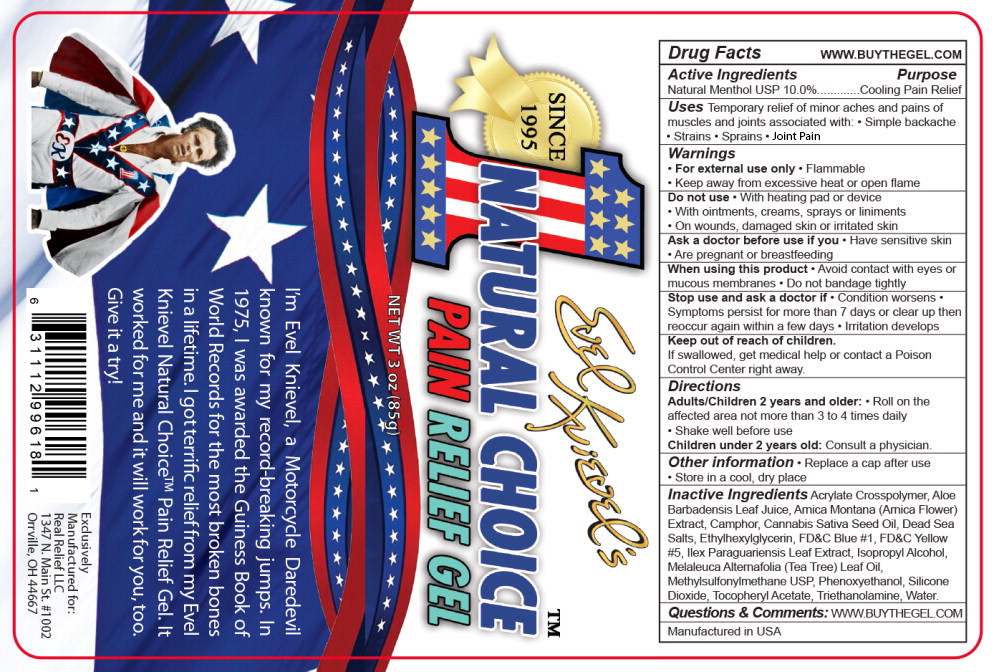 DRUG LABEL: Evel Knievels Natural Choice Pain Relief
NDC: 66902-195 | Form: GEL
Manufacturer: Natural Essentials, Inc.
Category: otc | Type: HUMAN OTC DRUG LABEL
Date: 20241021

ACTIVE INGREDIENTS: MENTHOL, UNSPECIFIED FORM 100 mg/1 g
INACTIVE INGREDIENTS: CARBOMER COPOLYMER TYPE A (ALLYL PENTAERYTHRITOL CROSSLINKED); CAMPHOR (SYNTHETIC); CANNABIS SATIVA SEED OIL; ETHYLHEXYLGLYCERIN; FD&C BLUE NO. 1; FD&C YELLOW NO. 5; ILEX PARAGUARIENSIS LEAF; ISOPROPYL ALCOHOL; TEA TREE OIL; DIMETHYL SULFONE; ALOE VERA LEAF; ARNICA MONTANA FLOWER; PHENOXYETHANOL; SILICON DIOXIDE; SODIUM CHLORIDE; .ALPHA.-TOCOPHEROL; TROLAMINE; WATER

Drug Facts

Active Ingredients

Natural Menthol USP 10.0%

Purpose

Cooling Pain Relief

Uses

Temporary relief of minor aches and pains of muscles and joints associated with:

- Simple backache
- Strains
- Sprains
- Joint Pain

Warnings

- For external use only
- Flammable
- Keep away from excessive heat or open flame

Do not use

- With heating pad or device
- With ointments, creams, sprays or liniments
- On wounds, damaged skin or irritated skin

Ask a doctor before use if you

- Have sensitive skin
- Are pregnant or breastfeeding

When using this product

- Avoid contact with eyes or mucous membranes
- Do not bandage tightly

Stop use and ask a doctor if

- Condition worsens
- Symptoms persist for more than 7 days or clear up then reoccur again within a few days
- Irritation develops

Keep out of reach of children.

If swallowed, get medical help or contact a Poison Control Center right away.

Directions

Adults/Children 2 years and older:

- Roll on the affected area not more than 3 to 4 times daily
- Shake well before use

Children under 2 years old:

Consult a physician.

Other information

- Replace a cap after use
- Store in a cool, dry place

Inactive Ingredients

Acrylate Crosspolymer, Aloe Barbadensis Leaf Juice, Arnica Montana (Arnica Flower) Extract, Camphor, Cannabis Sativa Seed Oil, Dead Sea Salts, Ethylhexylglycerin, FD&C Blue #1, FD&C Yellow #5, Ilex Paraguariensis Leaf Extract, Isopropyl Alcohol, Melaleuca Alternafolia (Tea Tree) Leaf Oil, Methylsulfonylmethane USP, Phenoxyethanol, Silicone Dioxide, Tocopheryl Acetate, Triethanolamine, Water.

Questions & Comments:

WWW.BUYTHEGEL.COM

Manufactured in USA

Principal Display Panel – Bottle Label

SINCE 1995

EVEL KNIEVEL'S

1 NATURAL CHOICE™

PAIN RELIEF GEL

NET WT 3 oz (85 g)